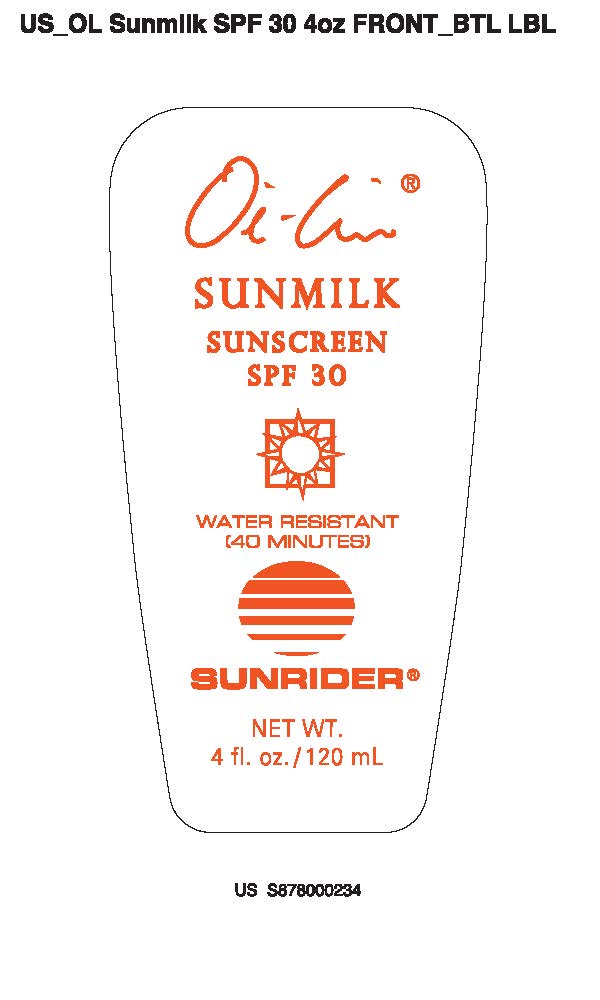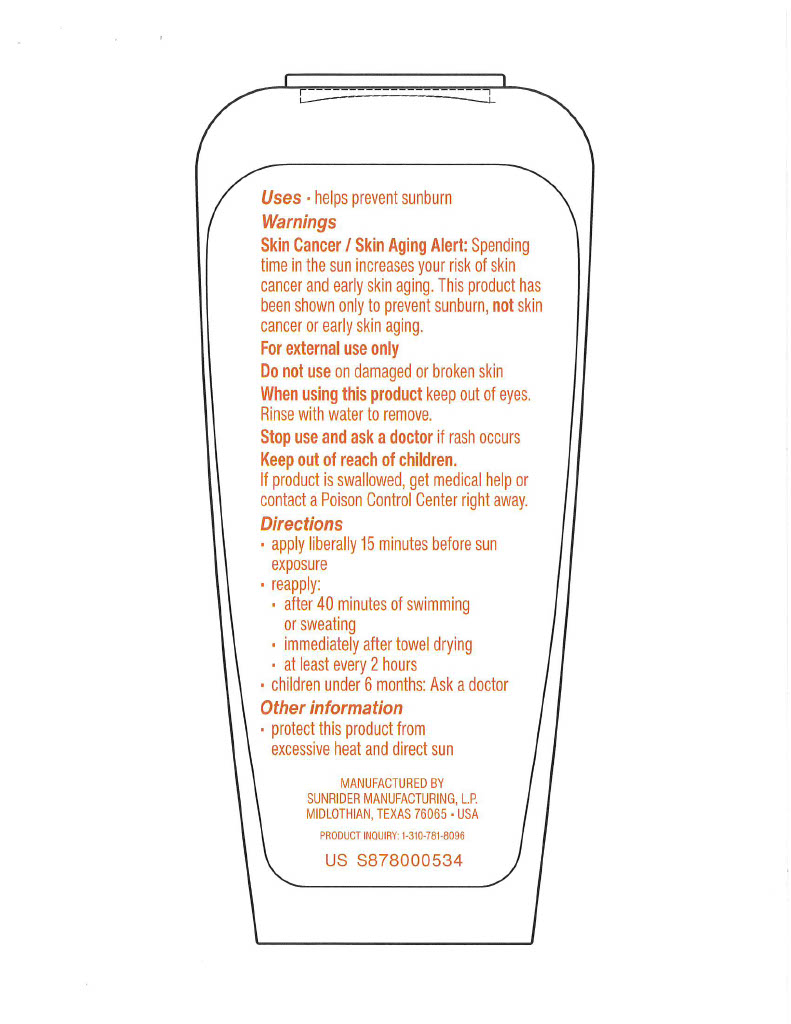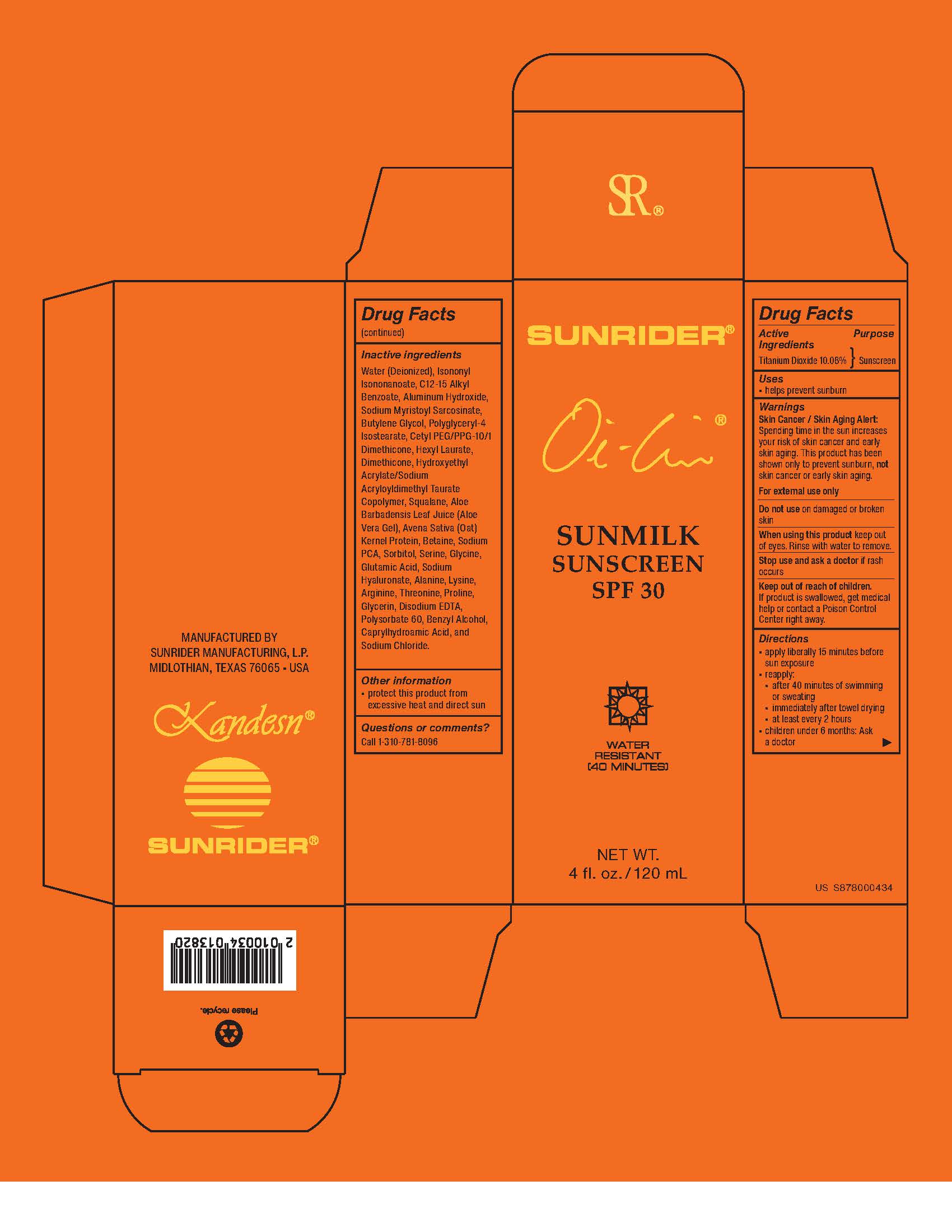 DRUG LABEL: OI LIN SUNMILK SUNSCREEN SPF 30
NDC: 62191-600 | Form: EMULSION
Manufacturer: Sunrider Manufacturing L.P.
Category: otc | Type: HUMAN OTC DRUG LABEL
Date: 20251229

ACTIVE INGREDIENTS: TITANIUM DIOXIDE 100.8 mg/1 g
INACTIVE INGREDIENTS: WATER; ISONONYL ISONONANOATE; C12-15 ALKYL BENZOATE; ALUMINUM HYDROXIDE; SODIUM MYRISTOYL SARCOSINATE; BUTYLENE GLYCOL; POLYGLYCERYL-4 ISOSTEARATE; CETYL PEG/PPG-10/1 DIMETHICONE (HLB 2); HEXYL LAURATE; DIMETHICONE; HYDROXYETHYL ACRYLATE/SODIUM ACRYLOYLDIMETHYL TAURATE COPOLYMER (45000 MPA.S AT 1%); SQUALANE; ALOE BARBADENSIS LEAF JUICE; OATMEAL; BETAINE; SODIUM PCA; SORBITOL; SERINE; GLYCINE; GLUTAMIC ACID; SODIUM HYALURONATE; ALANINE; LYSINE; ARGININE; THREONINE; PROLINE; GLYCERIN; EDETATE DISODIUM; POLYSORBATE 60; BENZYL ALCOHOL; CAPRYLHYDROXAMIC ACID; SODIUM CHLORIDE

OIL LIN® SUNMILK SUNSCREEN SPF 30

ACTIVE INGREDIENT: TITANIUM DIOXIDE 10.08%

INACTIVE INGREDIENT:

Water (Deionized)
Isononyl Isononanoate
C12-15 Alkyl Benzoate
Aluminum Hydroxide
Sodium Myristoyl Sarcosinate
Butylene Glycol
Polyglyceryl-4 Isostearate
Cetyl PEG/PPG-10/1 Dimethicone
Hexyl Laurate
Dimethione
Hydroxyethyl Acrylate/Sodium Acryloyldimethyl Taurate Copolymer
Squalane
Aloe Barbadensis Leaf Juice (Aloe Vera Gel)
Avena Sativa (Oat) Kernel Protein
Betaine
Sodium PCA
Sorbitol
Serine
Glycine
Glutamic Acid
Sodium Hyaluronate
Alanine
Lysine
Arginine
Threonine
Proline
Glycerin
Disodium EDTA
Polysorbate 60
Benzyl Alcohol
Caprylhydroamic Acid
Sodium Chloride

PURPOSE

USES: HELPS PREVENT SUNBURN.

INDICATIONS AND USAGE

Direction

- apply liberally 15 minutes before sun exposure.

reapply:

- After 40 minutes of swimming or sweating
- immediately after tower drying
- at least every 2 hours
- children under 6 months: Ask a doctor.

WARNING:

Skin Cancer/Skin Aging Alert:

Spending time in the sun increases your risk of skin cancer and early skin aging. This product has been shown only to prevent sunburn, not skin cancer or early skin aging.

For External use only

Do not useon damaged or broken skin.

When using this product keep out of eyes. Rinse with water to remove.

Stop use and ask a doctor if rash occurs.

If product is swallowed, get medical help or contact a Poison Control Center right away.

KEEP OUT OF REACH OF CHILDREN.

If prodcut is swallowed, get medical help or contact a Poison Control Center right away.